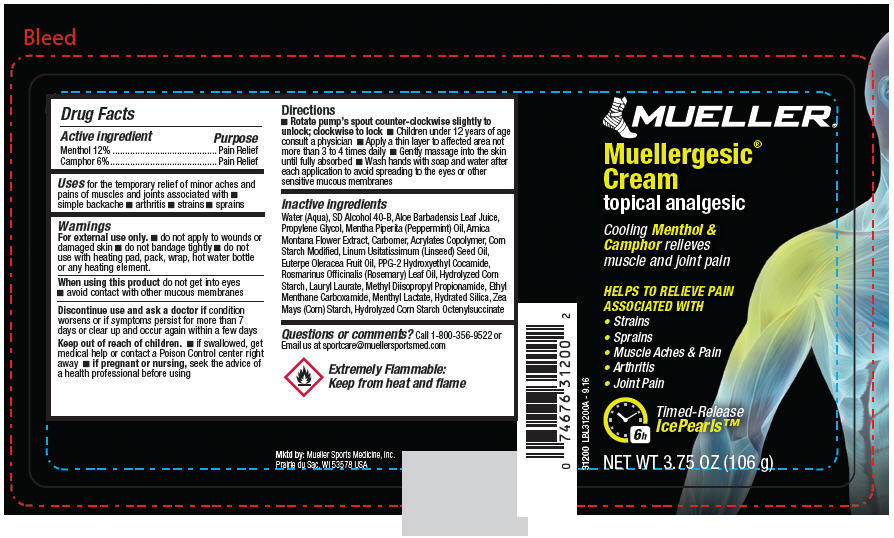 DRUG LABEL: Muellergesic
NDC: 52564-312 | Form: CREAM
Manufacturer: Mueller Sports Medicine LLC
Category: otc | Type: HUMAN OTC DRUG LABEL
Date: 20170208

ACTIVE INGREDIENTS: Menthol 12.72 g/106 g; Camphor (synthetic) 6.3 g/106 g
INACTIVE INGREDIENTS: WATER; ALOE VERA LEAF; PROPYLENE GLYCOL; PEPPERMINT OIL; ARNICA MONTANA FLOWER; CARBOXYPOLYMETHYLENE; LINSEED OIL; ACAI OIL; PPG-2 HYDROXYETHYL COCAMIDE; ROSEMARY OIL; LAURYL LAURATE; METHYL DIISOPROPYL PROPIONAMIDE; ETHYL MENTHANE CARBOXAMIDE, 1R,3R,4S; MENTHYL LACTATE, (-)-; HYDRATED SILICA; STARCH, CORN

Muellergesic®

Drug Facts

ACTIVE INGREDIENT

Active ingredient | Purpose
Menthol 12% | Pain Relief
Camphor 6% | Pain Relief

Uses

for the temporary relief of minor aches and pains of muscles and joints associated with

- simple backache
- arthritis
- strains
- sprains

Warnings

For external use only.

- do not apply to wounds or damaged skin
- do not bandage tightly
- do not use with heating pad, pack, wrap, hot water bottle or any heating element.

When using this product do not get into eyes

- avoid contact with other mucous membranes

STOP USE

Discontinue use and ask a doctor if condition worsens or if symptoms persist for more than 7 days or clear up and occur again within a few days

Keep out of reach of children.

- if swallowed, get medical help or contact a Poison Control center right away

PREGNANCY OR BREAST FEEDING

- if pregnant or nursing, seek the advice of a health professional before using

Directions

- Rotate pump's spout counter-clockwise slightly to unlock; clockwise to lock
- Children under 12 years of age consult a physician
- Apply a thin layer to affected area not more than 3 to 4 times daily
- Gently massage into the skin until fully absorbed
- Wash hands with soap and water after each application to avoid spreading to the eyes or other sensitive mucous membranes

Inactive ingredients

Water (Aqua), SD Alcohol 40-B, Aloe Barbadensis Leaf Juice, Propylene Glycol, Mentha Piperita (Peppermint) Oil, Arnica Montana Flower Extract, Carbomer, Acrylates Copolymer, Corn Starch Modified, Linum Usitatissimum (Linseed) Seed Oil, Euterpe Oleracea Fruit Oil, PPG-2 Hydroxyethyl Cocamide, Rosmarinus Officinalis (Rosemary) Leaf Oil, Hydrolyzed Corn Starch, Lauryl Laurate, Methyl Diisopropyl Propionamide, Ethyl Menthane Carboxamide, Menthyl Lactate, Hydrated Silica, Zea Mays (Corn) Starch, Hydrolyzed Corn Starch Octenylsuccinate

Questions or comments?

Call 1-800-356-9522 or Email us at sportcare@muellersportsmed.com

Extremely Flammable:
Keep from heat and flame

PRINCIPAL DISPLAY PANEL - 106 g Bottle Label

MUELLER®

Muellergesic®
Cream
topical analgesic

Cooling Menthol &
Camphor relieves
muscle and joint pain

HELPS TO RELIEVE PAIN
ASSOCIATED WITH

- Strains
- Sprains
- Muscle Aches & Pain
- Arthritis
- Joint Pain

Timed-Release
IcePearls™

6h

NET WT 3.75 OZ (106 g)

31200 LBL31200A - 9.16